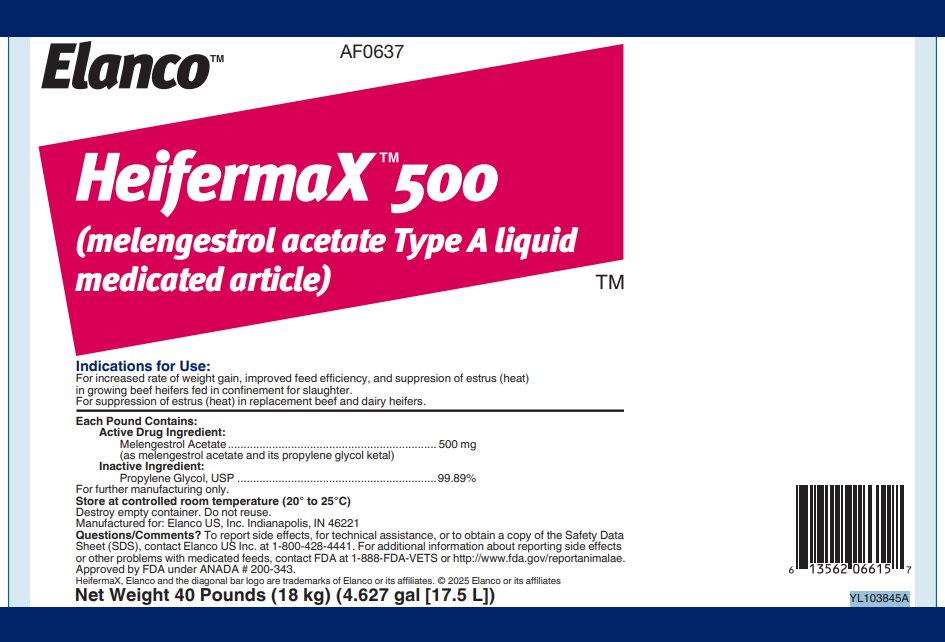 DRUG LABEL: Heifermax 500
NDC: 58198-0637 | Form: LIQUID
Manufacturer: Elanco US Inc.
Category: animal | Type: OTC ANIMAL DRUG LABEL
Date: 20260122

ACTIVE INGREDIENTS: melengestrol acetate 500 mg/0.45 kg

Elanco™

AF0637

HeifermaX™500

(melengestrol acetate Type A liquid medicated article)

Indications for Use:

For increased rate of weight gain, improved feed efficiency, and suppresion of estrus (heat) in growing beef heifers fed in confinement for slaughter.

For suppression of estrus (heat) in replacement beef and dairy heifers.

Each Pound Contains:

Active Drug Ingredient:
Melengestrol Acetate .................................................................. 500 mg
(as melengestrol acetate and its propylene glycol ketal)
Inactive Ingredient:
Propylene Glycol, USP ................................................................99.89%

For further manufacturing only.

Store at controlled room temperature (20° to 25°C)

Destroy empty container. Do not reuse.

Manufactured for: Elanco US, Inc. Indianapolis, IN 46221

Questions/Comments? To report side effects, for technical assistance, or to obtain a copy of the Safety Data Sheet (SDS), contact Elanco US Inc. at 1-800-428-4441. For additional information about reporting side effects or other problems with medicated feeds, contact FDA at 1-888-FDA-VETS or http://www.fda.gov/reportanimalae.

Approved by FDA under ANADA # 200-343.

HeifermaX, Elanco and the diagonal bar logo are trademarks of Elanco or its affiliates. © 2025 Elanco or its affiliates

Net Weight 40 Pounds (18 kg) (4.627 gal [17.5 L])

YL103845A

Elanco™

AF0637

HeifermaX™500

(melengestrol acetate Type A liquid medicated article)

DIRECTIONS FOR USE:

Growing beef heifers fed in confinement for slaughter.

HEIFERMAX 500 (melengestrol acetate Type A liquid medicated feed) should be thoroughly mixed in liquid Type C medicated feed which must be fed at 0.5 to 2 pounds per head daily to provide 0.25 to 0.5 mg of melengestrol acetate per head per day. Average daily intakes approximating the middle of this range provide the most optimal and economical improvements in rate of weight gain and feed utilization. Constant daily intakes of 0.35 to 0.5 mg per head per day give a high degree of estrus suppression. Levels of 0.25 to 0.35 mg provide a lower but still effective degree of estrus suppression.

Replacement beef and dairy heifers:

HEIFERMAX 500 should be thoroughly mixed in the supplement to provide 0.5 mg of melengestrol acetate per head per day.

ADDITIONAL RECOMMENDATIONS:

Not effective in steers and spayed heifers.

Growing beef heifers fed in confinement for slaughter:

Withdrawal periods of three to five days or more should be avoided to prevent the possibility that the heifers may come into estrus (heat) at loading time.

Replacement beef and dairy heifers:

Do not exceed 24 days of feeding of melengestrol acetate. A reduced conception rate can be expected if heifers are bred at estruses observed within 1 to 12 days after withdrawal of melengestrol acetate, whereas heifers bred at subsequent observed estruses are expected to have normal conception rates.

MIXING DIRECTIONS:

Liquid Type B and C medicated feeds containing melengestrol acetate must have a pH of 4 to 8 and their labels must bear appropriate mixing directions. Mixing directions for liquid Type B or C feeds stored in recirculation tank systems are: “Recirculate immediately prior to use for no less than 10 minutes, moving not less than 1 percent of the tank contents per minute from the bottom of the tank to the top. Recirculate daily, as directed in this paragraph even when the Type B (or C) feed is not used.” Mixing directions for liquid Type B and C feeds stored in mechanical, air or other agitation-type tank systems are: “Agitate immediately prior to use for not less than 10 minutes, creating a turbulence at the bottom of the tank that is visible at the top. Agitate daily, as directed in this paragraph, even when the Type B (or C) feed is not used.”

Intermediate medicated feeds should not be made from HEIFERMAX 500 except as a part of a continuous mixing operation to make a complete liquid Type B or Type C medicated feed.

Thoroughly mix 0.5 to 4 pounds of HEIFERMAX 500 per ton of a non-medicated feed to prepare a Type C medicated feed containing 0.25 to 2 grams of melengestrol acetate per ton. The following Table may be used as a guide in determining the amount of HEIFERMAX 500 to be added to prepare a ton of Type C medicated feed.

 |  | HEIFERMAX 500 Per Ton of Type C Feed
Amount of Type C Feed Fed (lb/head/day) | Melengestrol Acetate (mg/head/day) | When Added by Weight (lb) | When Added by Volume (mL)
0.5 | 0.25 | 2 | 876
0.5 | 0.3 | 2.4 | 1,051
0.5 | 0.35 | 2.8 | 1,226
0.5 | 0.4 | 3.2 | 1,402
0.5 | 0.45 | 3.6 | 1,577
0.5 | 0.5 | 4 | 1,752
1 | 0.25 | 1 | 438
1 | 0.3 | 1.2 | 526
1 | 0.35 | 1.4 | 613
1 | 0.4 | 1.6 | 701
1 | 0.45 | 1.8 | 788
1 | 0.5 | 2 | 876
1.5 | 0.25 | 0.66 | 289
1.5 | 0.3 | 0.8 | 350
1.5 | 0.35 | 0.93 | 407
1.5 | 0.4 | 1.07 | 469
1.5 | 0.45 | 1.2 | 526
1.5 | 0.5 | 1.33 | 582
2 | 0.25 | 0.5 | 219
2 | 0.3 | 0.6 | 263
2 | 0.35 | 0.7 | 307
2 | 0.4 | 0.8 | 350
2 | 0.45 | 0.9 | 394
2 | 0.5 | 1 | 438

Type B medicated feed containing 4 to 10 grams melengestrol acetate per ton may be manufactured by thoroughly mixing 8 to 20 lbs of HEIFERMAX 500 (melengestrol acetate Type A liquid medicated feed) with 1,992 to 1,980 lbs of non-medicated feed. Labeling for such Type B feed shall contain directions for manufacturing Type C medicated feeds containing 0.25 to 2 grams melengestrol acetate per ton (0.125 to 1 mg/lb). The Type C medicated feed, containing melengestrol acetate, must be top dressed on grain or roughage or mixed with a complete ration at the rate of 0.5 to 2 pounds per head per day.

Good manufacturing practice regulations must be adhered to in manufacturing feeds containing HEIFERMAX 500.

Restricted Drug — Use only as Directed (California)

Product of Spain

WITHDRAWAL PERIOD:

No withdrawal period is required when used according to labeling.

User Safety Warnings: Not for use in humans. Keep out of reach of children.

YL103845B

Principal Display Panel - 40 lb Carton Label

Elanco™

AF0637

HeifermaX™500

(melengestrol acetate Type A liquid medicated article)

Indications for Use:

For increased rate of weight gain, improved feed efficiency, and suppresion of estrus (heat)
in growing beef heifers fed in confinement for slaughter.
For suppression of estrus (heat) in replacement beef and dairy heifers.

Each Pound Contains:

Active Drug Ingredient:
Melengestrol Acetate .................................................................. 500 mg
(as melengestrol acetate and its propylene glycol ketal)
Inactive Ingredient:
Propylene Glycol, USP ................................................................99.89%

For further manufacturing only.

Store at controlled room temperature (20° to 25°C)

Destroy empty container. Do not reuse.

Manufactured for: Elanco US, Inc. Indianapolis, IN 46221

Questions/Comments? To report side effects, for technical assistance, or to obtain a copy of the Safety Data
Sheet (SDS), contact Elanco US Inc. at 1-800-428-4441. For additional information about reporting side effects
or other problems with medicated feeds, contact FDA at 1-888-FDA-VETS or http://www.fda.gov/reportanimalae.

Approved by FDA under ANADA # 200-343.

HeifermaX, Elanco and the diagonal bar logo are trademarks of Elanco or its affiliates. © 2025 Elanco or its affiliates

Net Weight 40 Pounds (18 kg) (4.627 gal [17.5 L])

YL103845A